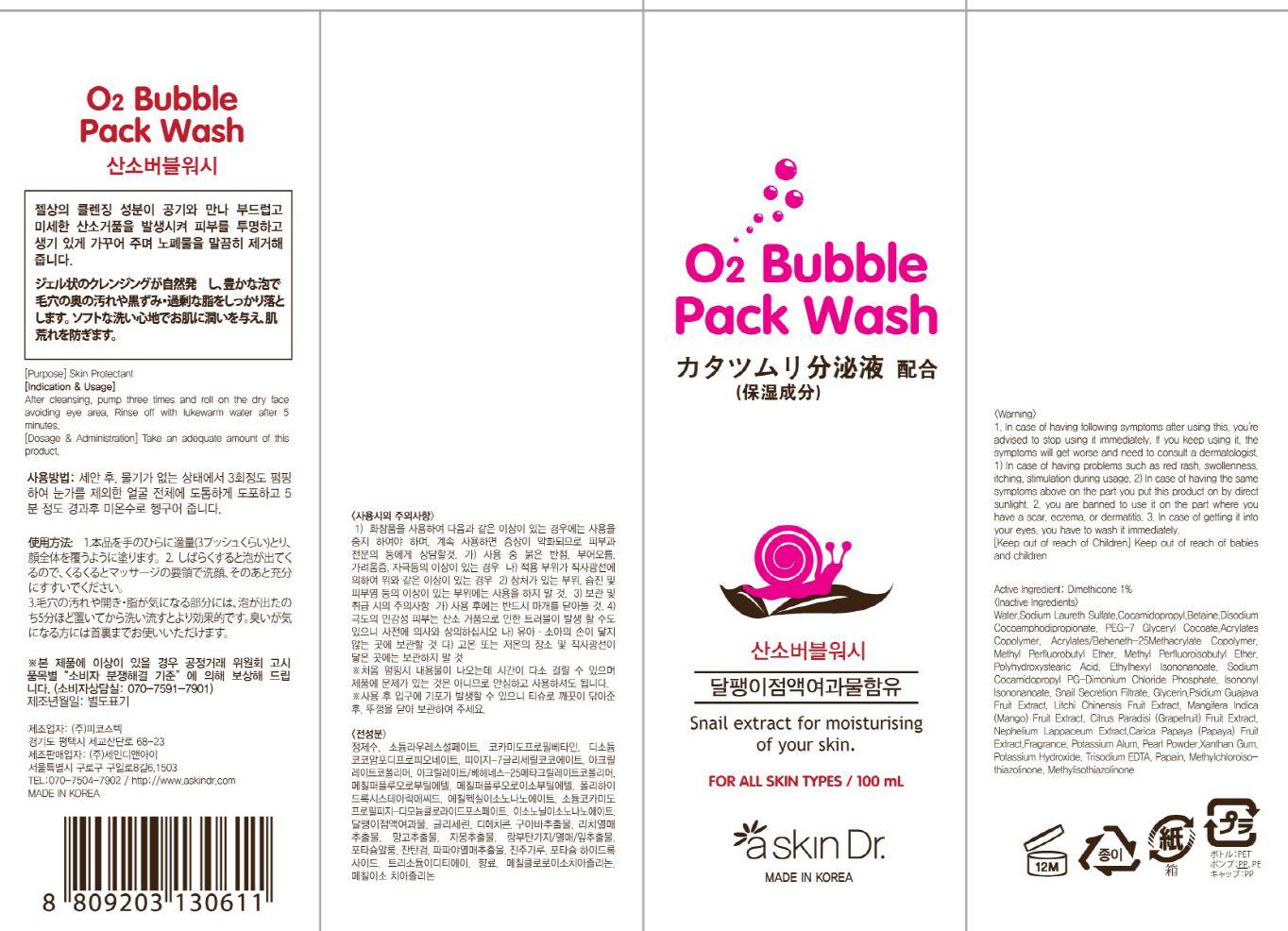 DRUG LABEL: O2 Bubble Pack Wash
NDC: 69072-030 | Form: LIQUID
Manufacturer: Seindni Co.,ltd
Category: otc | Type: HUMAN OTC DRUG LABEL
Date: 20181210

ACTIVE INGREDIENTS: Dimethicone 1 mg/100 mL
INACTIVE INGREDIENTS: Water; Betaine

ACTIVE INGREDIENT

Active Ingredients: Dimethicone 1%

INACTIVE INGREDIENT

Inactive Ingredients:
Water,Sodium Laureth Sulfate,Cocamidopropyl,Betaine,Disodium Cocoamphodipropionate,PEG-7 Glyceryl Cocoate,Acrylates Copolymer,Acrylates/Beheneth-25 Methacrylate Copolymer,Methyl Perfluorobutyl Ether,Methyl Perfluoroisobutyl Ether,Polyhydroxystearic Acid,Ethylhexyl Isononanoate,Sodium Cocamidopropyl PG-Dimonium Chloride Phosphate,Isononyl Isononanoate,Snail Secretion Filtrate, Glycerin,Psidium Guajava Fruit Extract,Litchi Chinensis Fruit Extract,Mangifera Indica (Mango) Fruit Extract, Citrus Paradisi (Grapefruit) Fruit Extract,Nephelium Lappaceum Extract,Carica Papaya (Papaya) Fruit Extract,Fragrance,Potassium Alum,Pearl Powder,Xanthan Gum,Potassium Hydroxide,Trisodium EDTA, Papain,Methylchloroisothiazolinone,Methylisothiazolinone

PURPOSE

Purpose: Skin Protectant

WARNINGS

Warning:
1. In case of having following symptoms after using this, you're advised to stop using it immediately. If you keep using it, the symptoms will get worse and need to consult a dermatologist. 1) In case of having problems such as red rash, swollenness, itching, stimulation during usage. 2) In case of having the same symptoms above on the part you put this product on by direct sunlight. 2. you are banned to use it on the part where you have a scar, eczema, or dermatitis. 3. In case of getting it into your eyes, you have to wash it immediately.

Keep out of reach of Children: Keep out of reach of babies and children

INDICATIONS AND USAGE

Indication and Usage: After cleansing, pump three times and roll on the dry face avoiding eye area. Rinse off with lukewarm water after 5 minutes.

Dosage and Administration : Take an adequate amount of this product.